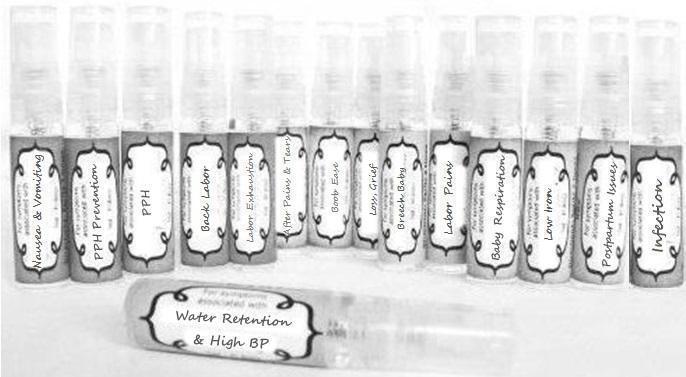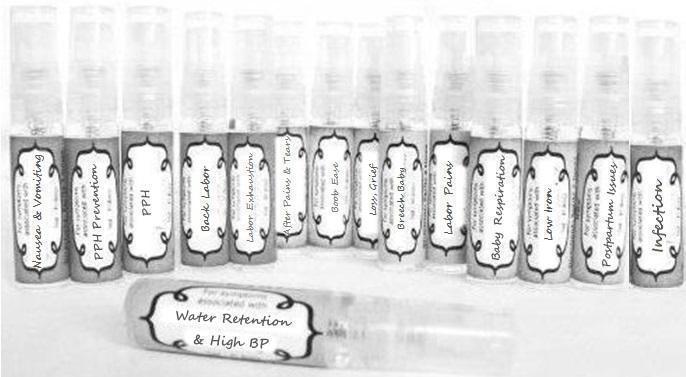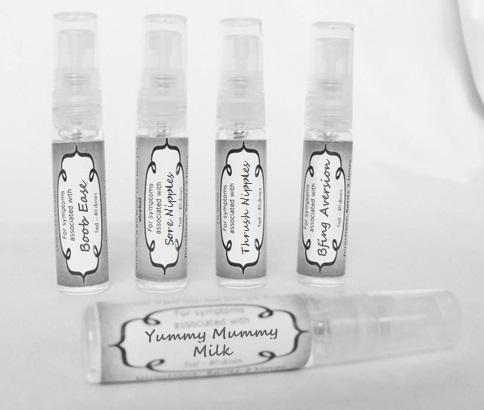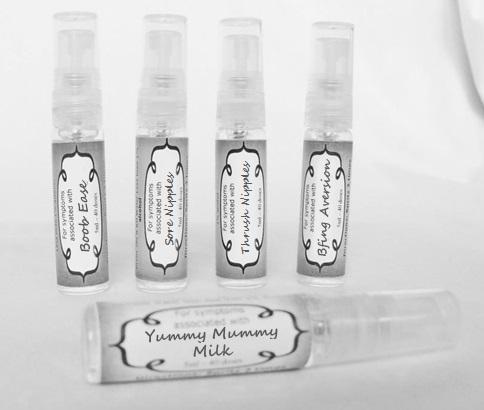 DRUG LABEL: Nausea and Vomiting
NDC: 59667-0043 | Form: SPRAY
Manufacturer: Home Sweet Homeopathics
Category: homeopathic | Type: HUMAN OTC DRUG LABEL
Date: 20130802

ACTIVE INGREDIENTS: ACONITUM NAPELLUS 30 [hp_C]/30 [hp_C]; ARSENIC ACID 30 [hp_C]/30 [hp_C]; ASARUM CANADENSE ROOT 30 [hp_C]/30 [hp_C]; CONIUM MACULATUM FLOWERING TOP 30 [hp_C]/30 [hp_C]; IPECAC 30 [hp_C]/30 [hp_C]; WOOD CREOSOTE 30 [hp_C]/30 [hp_C]; LACTIC ACID, DL- 30 [hp_C]/30 [hp_C]; GONORRHEAL URETHRAL SECRETION HUMAN 30 [hp_C]/30 [hp_C]; SODIUM CHLORIDE 30 [hp_C]/30 [hp_C]; NUTMEG 30 [hp_C]/30 [hp_C]; STRYCHNOS NUX-VOMICA SEED 30 [hp_C]/30 [hp_C]; PHOSPHORUS 30 [hp_C]/30 [hp_C]; PULSATILLA VULGARIS 30 [hp_C]/30 [hp_C]; SEPIA OFFICINALIS JUICE 30 [hp_C]/30 [hp_C]; TOBACCO LEAF 30 [hp_C]/30 [hp_C]; NICOTINE 30 [hp_C]/30 [hp_C]
INACTIVE INGREDIENTS: WATER; ALCOHOL

PURPOSE

For symptoms associated with

To be used according to label indications.

Directions:

Spritz 1 time under the tongue 3 x per day until improvement is seen, dose once each time symptoms return.

Keep out of reach of children.

WARNINGS

If no improvement is seen after 7 days or new symptoms develop, discontinue use.

Active ingredients:

listed for each remedy.

Inactive Ingredients:

In reverse osmosis water with less than 1% alcohol.